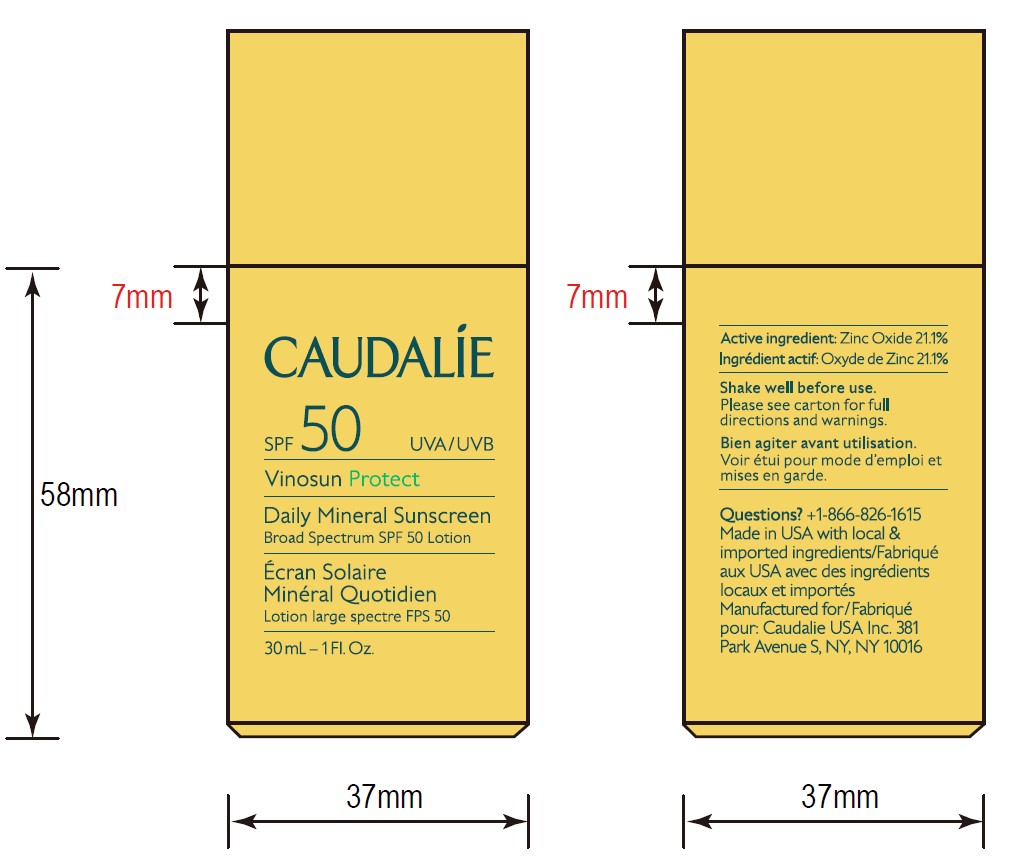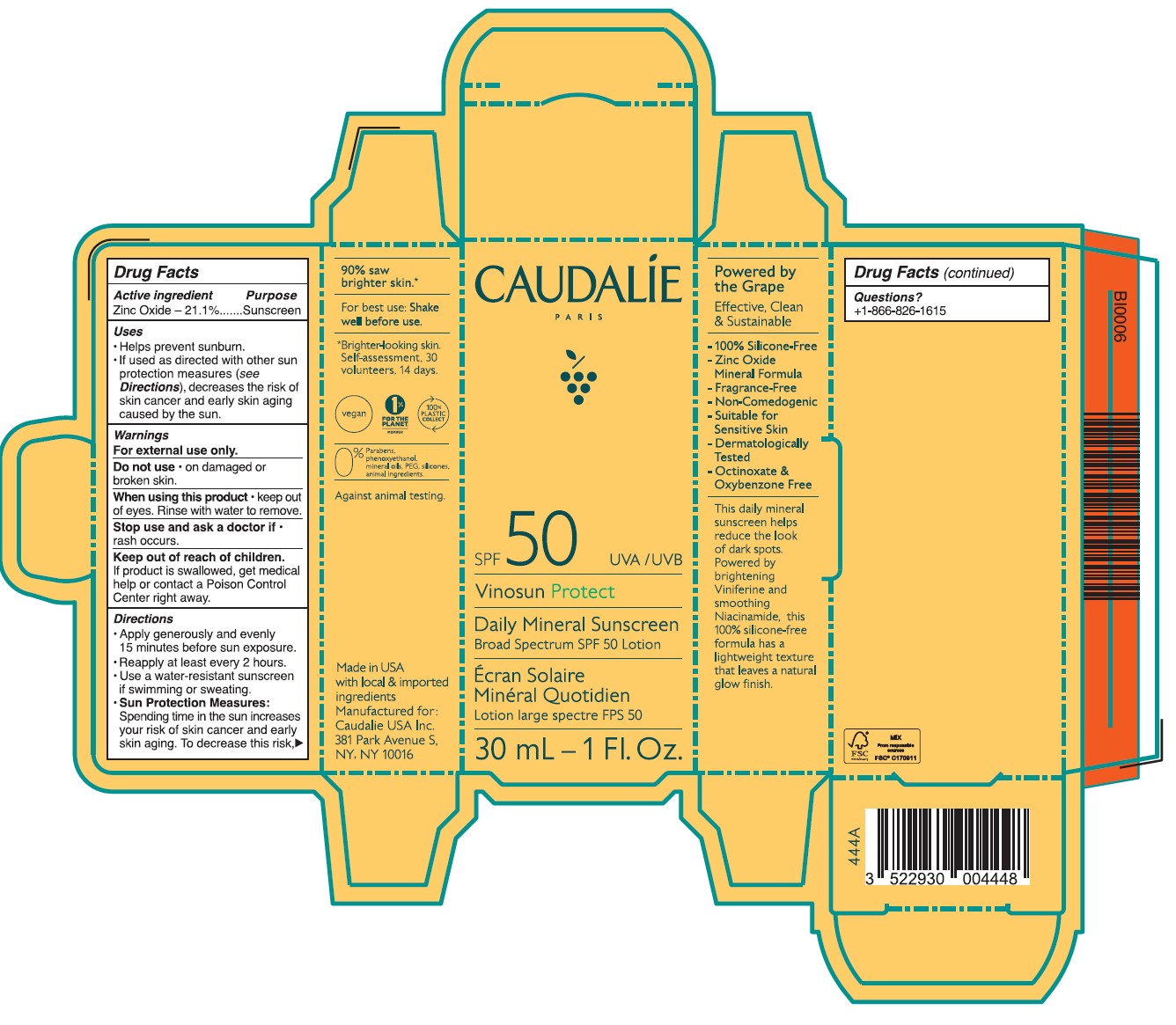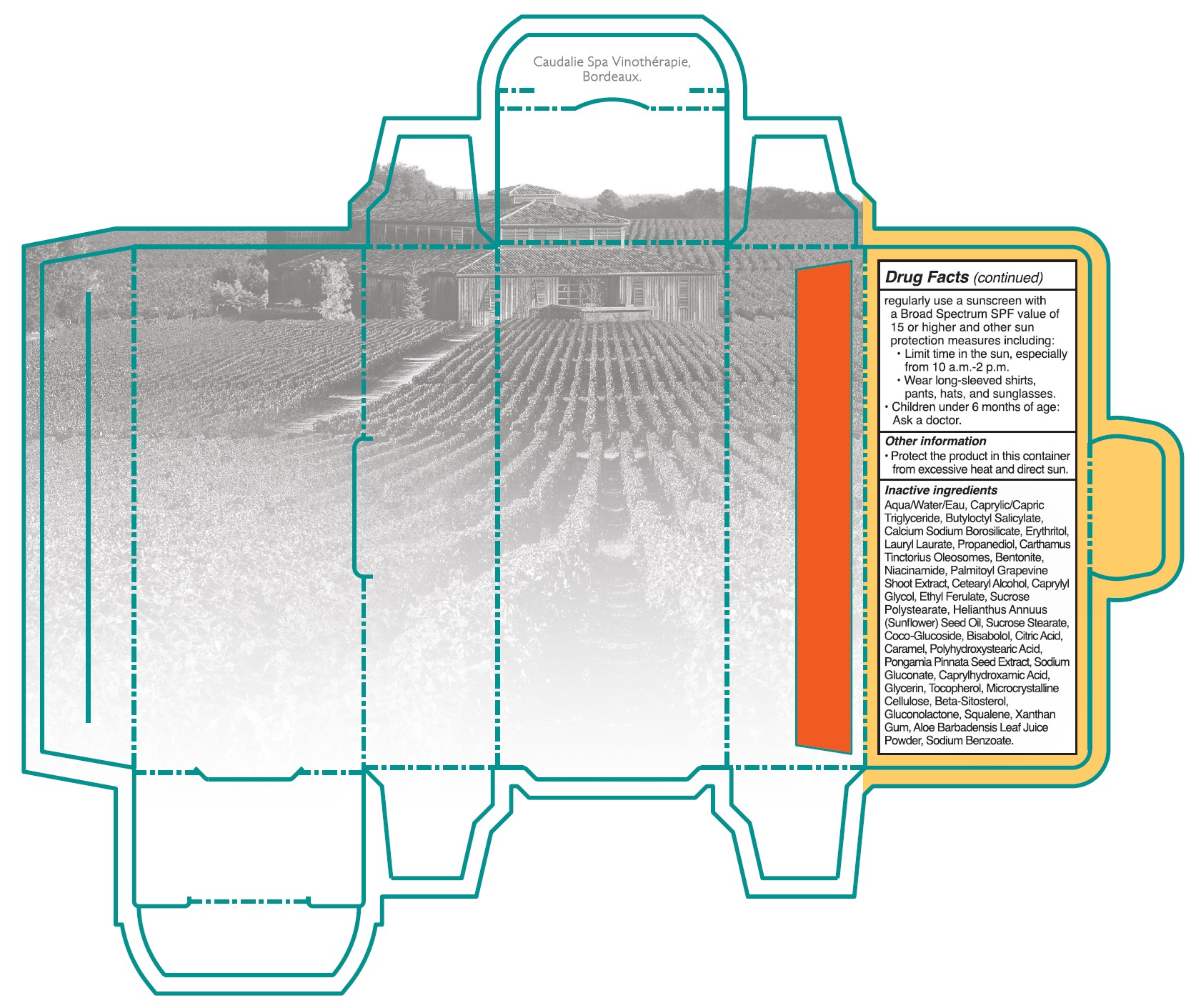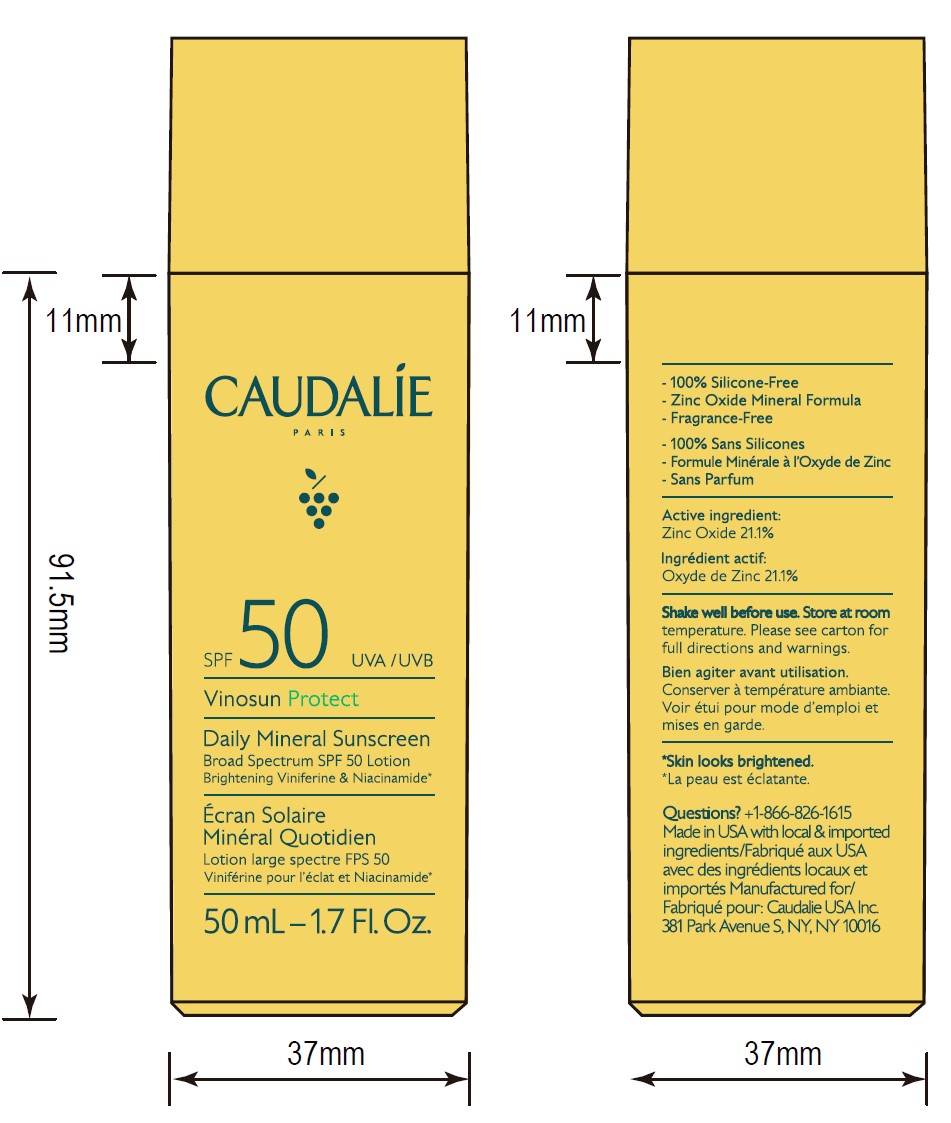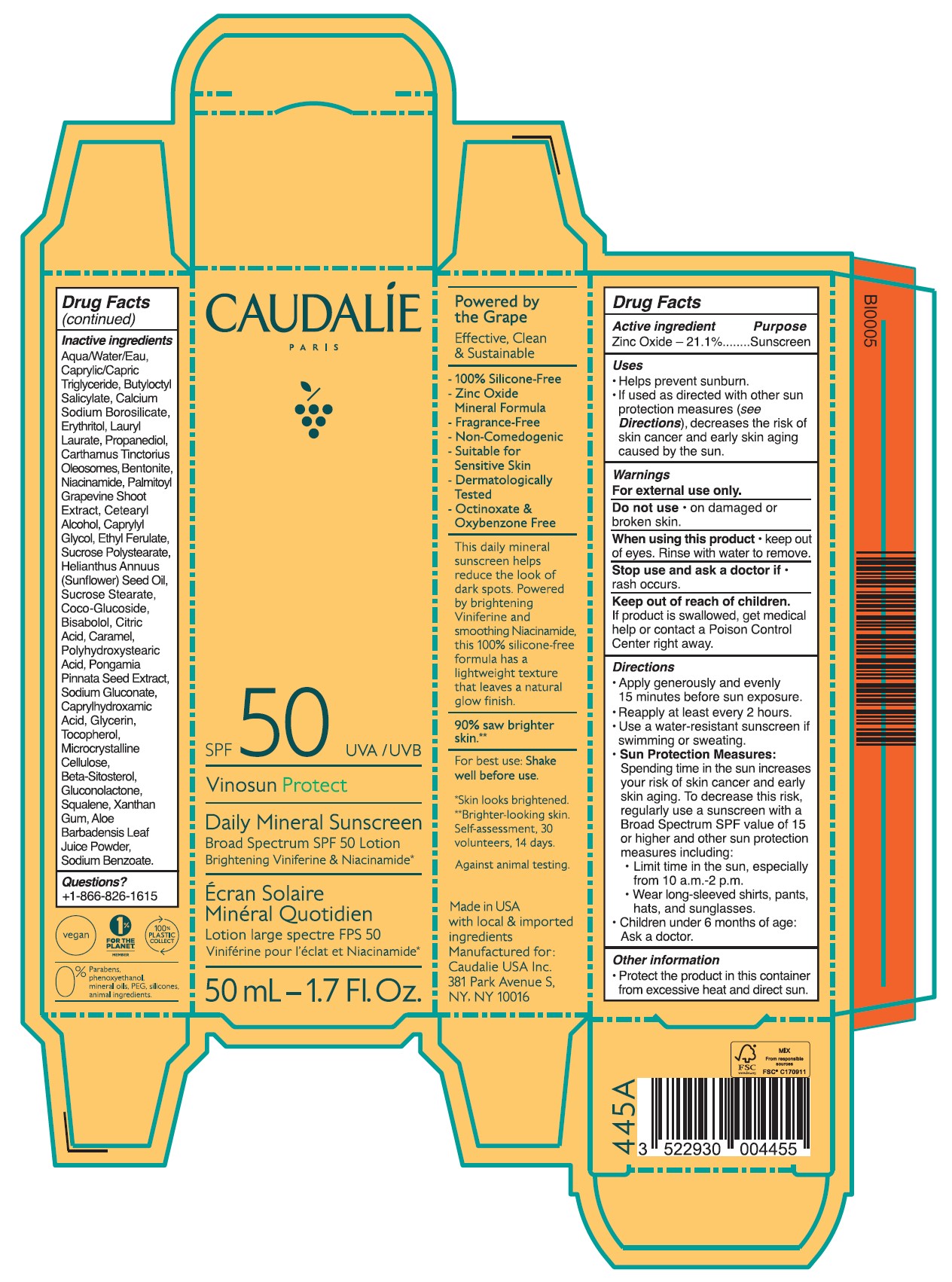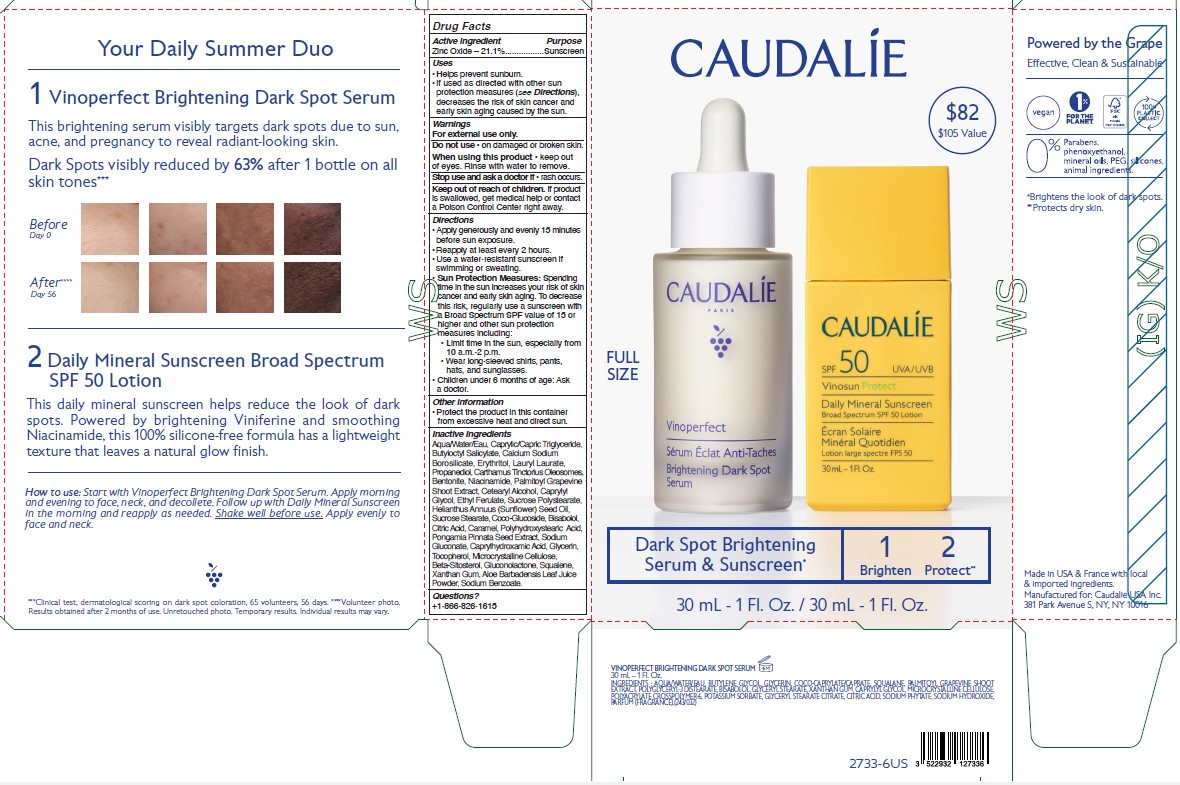 DRUG LABEL: CAUDALIE Daily Mineral Sunscreen Broad Spectrum SPF 50
NDC: 76296-060 | Form: LOTION
Manufacturer: Caudalie USA, Inc.
Category: otc | Type: HUMAN OTC DRUG LABEL
Date: 20241129

ACTIVE INGREDIENTS: ZINC OXIDE 13.1875 g/62.5 g
INACTIVE INGREDIENTS: PROPANEDIOL; CARTHAMUS TINCTORIUS SEED OLEOSOMES; CAPRYLHYDROXAMIC ACID; GLYCERIN; NIACINAMIDE; BUTYLOCTYL SALICYLATE; LEVOMENOL; .BETA.-SITOSTEROL; GLUCONOLACTONE; SODIUM BENZOATE; CITRIC ACID MONOHYDRATE; CARAMEL; PONGAMIA PINNATA SEED; XANTHAN GUM; BOROSILICATE GLASS; SODIUM GLUCONATE; TOCOPHEROL; MICROCRYSTALLINE CELLULOSE; MEDIUM-CHAIN TRIGLYCERIDES; ALOE VERA LEAF; SUNFLOWER OIL; ERYTHRITOL; POLYHYDROXYSTEARIC ACID (2300 MW); LAURYL LAURATE; WATER; BENTONITE; ETHYL FERULATE; COCO GLUCOSIDE; CAPRYLYL GLYCOL; SUCROSE STEARATE; SQUALENE; CETOSTEARYL ALCOHOL

CAUDALIE Daily Mineral Sunscreen Broad Spectrum SPF 50 Lotion

Active ingredient Purpose

Zinc Oxide 21.1% ...... Sunscreen

Uses

- helps prevent sunburn.
- if used as directed with other sun protection measures (see Directions), decreases the risk of skin cancer and early skin aging caused by the sun.

Warnings

For external use only.

When using this product • keep out of eyes. Rinse with water to remove.

Stop use and ask a doctor if • rash occurs.

Keep out of reach of children. If product is swallowed, get medical help or contact a Poison Control Center right away.

Directions

• Apply generously and evenly 15 minutes before sun exposure.

• Reapply at least every 2 hours • Use a water-resistant sunscreen if swimming or sweating.

• Sun Protection Measures. Spending time in the sun increases your risk of skin cancer and early skin aging. To decrease this risk, regulalry use a sunscreen with a Broad Spectrum SPF value of 15 or higher and other sun protection measures including:

•Limit time in the sun, especially from 10 a.m. - 2 p.m.

•Wear long-sleeved shirts, pants, hats, and singlasses.

•Children under 6 months of age: Ask a doctor.

Other information

• Protect the product in this contaner from excessive heat and direct sun.

Inactive ingredients

Aqua/Water/Eau, Caprylic/Capric Triglyceride, Butyloctyl Salicylate, Calcium Sodium Borosilicate, Erythritol, Lauryl Laurate, Propanediol, Carthamus Tinctorius Oleosomes, Bentonite, Niacinamide, Palmitoyl Grapevine Shoot Extract, Cetearyl Alcohol, Caprylyl Glycol, Ethyl Ferulate, Sucrose Polystearate, Helianthus Annuus (Sunflower) Seed Oil,Sucrose Stearate, Coco-Glucoside, Bisabolol, Citric Acid, Caramel, Polyhydroxystearic Acid, Pongamia Pinnata Seed Extract, Sodium Gluconate, Caprylhydroxamic Acid, Glycerin, Tocopherol, Microcrystallnine Cellulose, Beta-Sitosterol, Gluconolactone, Squalene, Xanthan Gum, Aloe Barbadensis Leaf Juice Powder, Sodium Benzoate.

Questions?

+1-866-826-1615